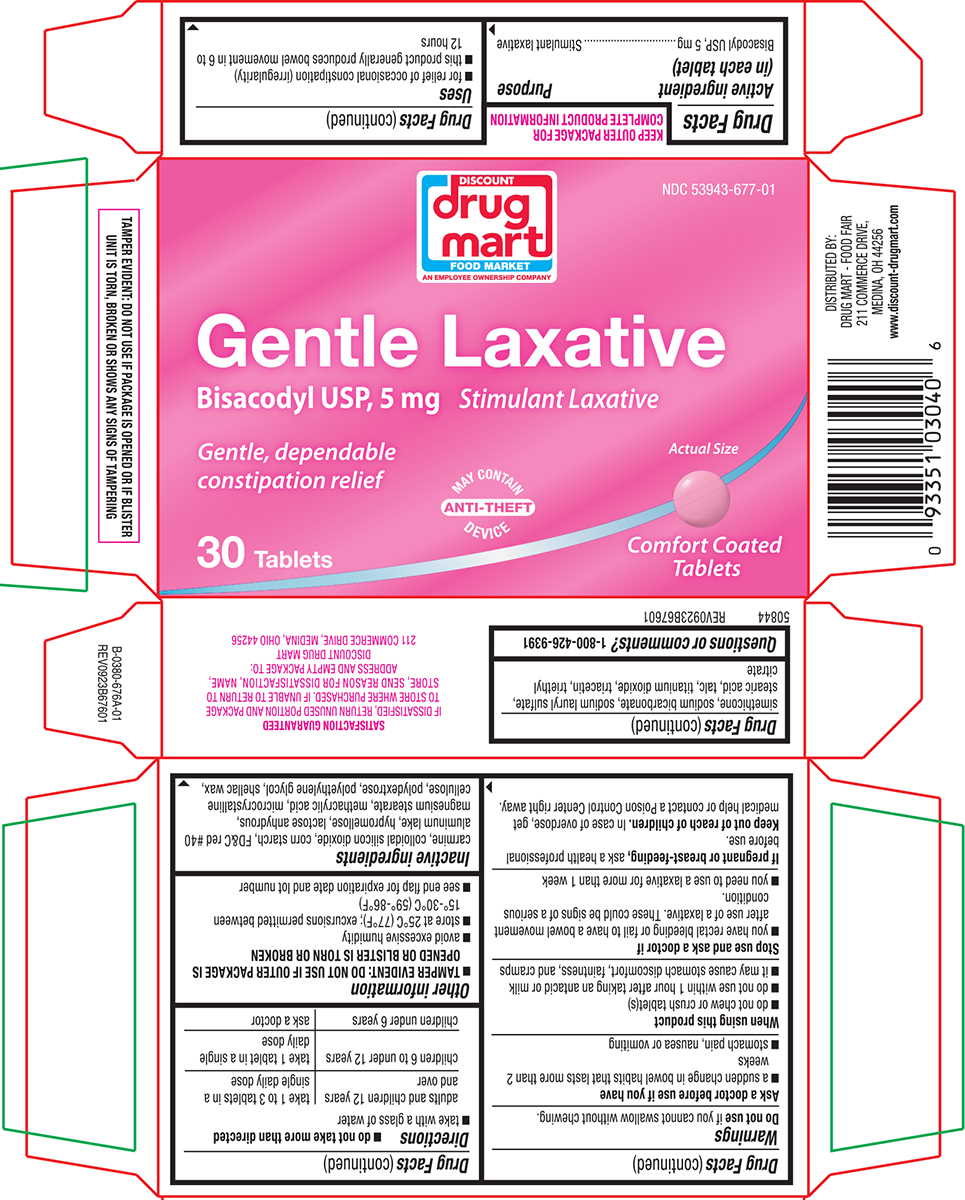 DRUG LABEL: Gentle Laxative
NDC: 53943-677 | Form: TABLET, DELAYED RELEASE
Manufacturer: Discount Drug Mart
Category: otc | Type: HUMAN OTC DRUG LABEL
Date: 20251210

ACTIVE INGREDIENTS: BISACODYL 5 mg/1 1
INACTIVE INGREDIENTS: SILICON DIOXIDE; STARCH, CORN; FD&C RED NO. 40 ALUMINUM LAKE; HYPROMELLOSE, UNSPECIFIED; ANHYDROUS LACTOSE; MAGNESIUM STEARATE; METHACRYLIC ACID; MICROCRYSTALLINE CELLULOSE; POLYDEXTROSE; POLYETHYLENE GLYCOL, UNSPECIFIED; SHELLAC; DIMETHICONE; WATER; SODIUM BICARBONATE; SODIUM LAURYL SULFATE; STEARIC ACID; TALC; TITANIUM DIOXIDE; TRIACETIN; TRIETHYL CITRATE

Drug Mart 44-676A Gentle

Active ingredient (in each tablet)

Bisacodyl USP, 5 mg

Purpose

Stimulant laxative

Uses

- for relief of occasional constipation (irregularity)
- this product generally produces bowel movement in 6 to 12 hours

Warnings

Do not use

if you cannot swallow without chewing.

Ask a doctor before use if you have

- a sudden change in bowel habits that lasts more than 2 weeks
- stomach pain, nausea or vomiting

When using this product

- do not chew or crush tablet(s)
- do not use within 1 hour after taking an antacid or milk
- it may cause stomach discomfort, faintness, and cramps

Stop use and ask a doctor if

- you have rectal bleeding or fail to have a bowel movement after use of a laxative. These could be signs of a serious condition.
- you need to use a laxative for more than 1 week

If pregnant or breast-feeding,

ask a health professional before use.

Keep out of reach of children.

In case of overdose, get medical help or contact a Poison Control Center right away.

Directions

- do not take more than directed
- take with a glass of water

adults and children 12 years and over | take 1 to 3 tablets in a single daily dose
children 6 to under 12 years | take 1 tablet in a single daily dose
children under 6 years | ask a doctor

Other information

- TAMPER EVIDENT: DO NOT USE IF OUTER PACKAGE IS OPENED OR BLISTER IS TORN OR BROKEN
- avoid excessive humidity
- store at 25ºC (77ºF); excursions permitted between 15º-30ºC (59º-86ºF)
- see end flap for expiration date and lot number

Inactive ingredients

carmine, colloidal silicon dioxide, corn starch, FD&C red #40 aluminum lake, hypromellose, lactose anhydrous, magnesium stearate, methacrylic acid, microcrystalline cellulose, polydextrose, polyethylene glycol, shellac wax, simethicone, sodium bicarbonate, sodium lauryl sulfate, stearic acid, talc, titanium dioxide, triacetin, triethyl citrate

Questions or comments?

1-800-426-9391

Principal Display Panel

NDC 53943-677-01

DISCOUNT
drug
mart
FOOD MARKET
AN EMPLOYEE OWNERSHIP COMPANY

Gentle Laxative
Bisacodyl USP, 5 mg
Stimulant Laxative

Gentle, dependable
constipation relief

30 Tablets

MAY CONTAIN
ANTI-THEFT
DEVICE

Actual Size

Comfort Coated
Tablets

TAMPER EVIDENT: DO NOT USE IF PACKAGE IS OPENED OR IF BLISTER
UNIT IS TORN, BROKEN OR SHOWS ANY SIGNS OF TAMPERING

DISTRIBUTED BY:
DRUG MART - FOOD FAIR
211 COMMERCE DRIVE,
MEDINA, OH 44256
www.discount-drugmart.com

SATISFACTION GUARANTEED
IF DISSATISFIED, RETURN UNUSED PORTION AND PACKAGE
TO STORE WHERE PURCHASED. IF UNABLE TO RETURN TO
STORE, SEND REASON FOR DISSATISFACTION, NAME,
ADDRESS AND EMPTY PACKAGE TO:
DISCOUNT DRUG MART
211 COMMERCE DRIVE, MEDINA, OHIO 44256

50844 REV0923B67601

Discount Drug Mart 44-676A